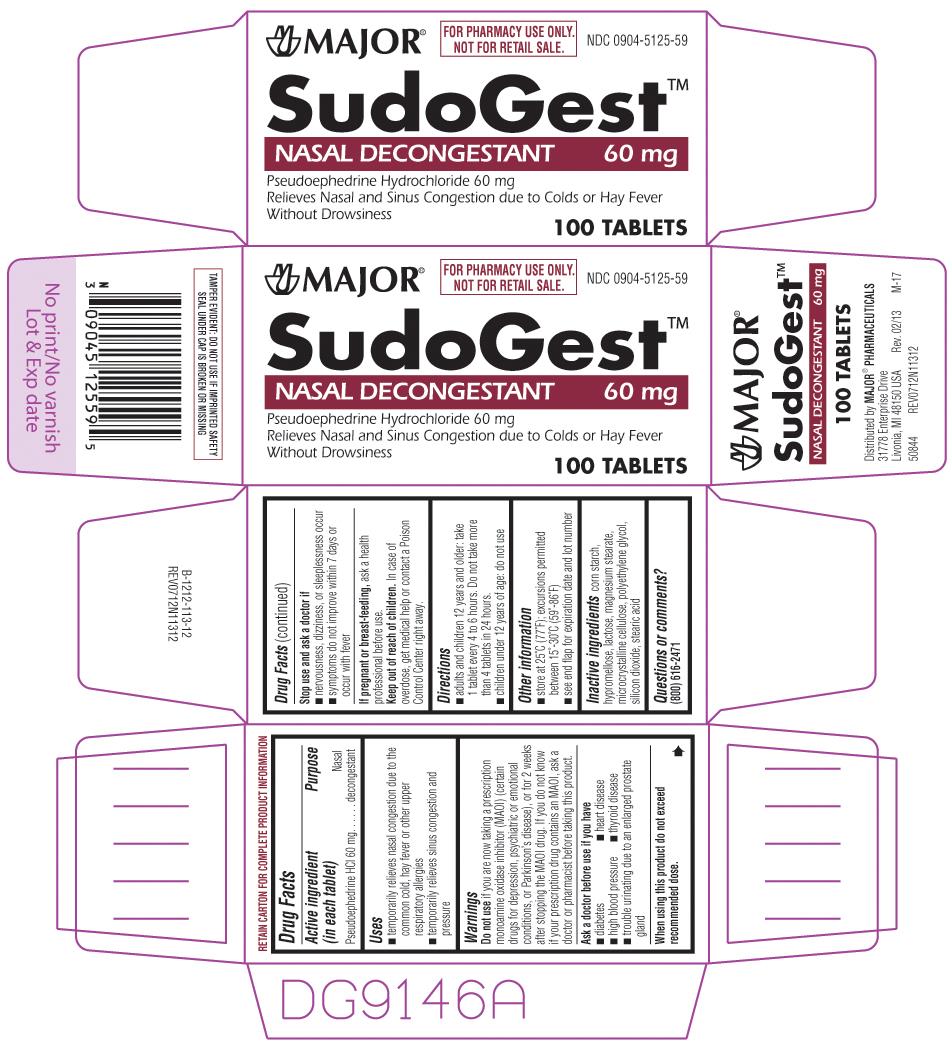 DRUG LABEL: SudoGest
NDC: 33261-651 | Form: TABLET, FILM COATED
Manufacturer: Aidarex Pharmaceuticals LLC
Category: otc | Type: HUMAN OTC DRUG LABEL
Date: 20130522

ACTIVE INGREDIENTS: PSEUDOEPHEDRINE HYDROCHLORIDE 60 mg/1 1
INACTIVE INGREDIENTS: HYPROMELLOSES; LACTOSE; MAGNESIUM STEARATE; POLYETHYLENE GLYCOLS; SILICON DIOXIDE; STEARIC ACID; CELLULOSE, MICROCRYSTALLINE

SudoGest
Nasal Decongestant

Active ingredient (in each tablet)

Pseudoephedrine HCl 60 mg

Purpose

Nasal decongestant

Uses

- temporarily relieves nasal congestion due to the common cold, hay fever or other upper respiratory allergies
- temporarily relieves sinus congestion and pressure

Warnings

Do not use

if you are now taking a prescription monoamine oxidase inhibitor (MAOI) (certain drugs for depression, psychiatric or emotional conditions, or Parkinson's disease), or for 2 weeks after stopping the MAOI drug. If you do not know if your prescription drug contains an MAOI, ask a doctor or pharmacist before taking this product.

Ask a doctor before use if you have

- diabetes
- thyroid disease
- heart disease
- high blood pressure
- trouble urinating due to enlargement of the prostate gland

When using this product

do not exceed recommended dose.

Stop use and ask a doctor if

- nervousness, dizziness, or sleeplessness occur
- symptoms do not improve within 7 days or occur with fever

If pregrant or breast-feeding,

ask a health professional before use.

Keep out of reach of children.

In case of overdose, get medical help or contact a Poison Control Center right away.

Directions

- adults and children 12 years and older: take 1 tablet every 4 to 6 hours. Do not take more than 4 tablets in 24 hours.
- children under 12 years of age: do not use

Other information

- store at 25ºC (77ºF); excursions permitted between 15˚-30˚C (59˚-86˚F)
- see end flap for expiration date and lot number

Inactive ingredients

corn starch, hypromellose, lactose, magnesium stearate, microcrystalline cellulose, polyethylene glycol, silicon dioxide, stearic acid

Questions or comments?

(800)-616-2471

Principal display panel

MAJOR®

FOR PHARMACY USE ONLY.
NOT FOR RETAIL SALE.

NDC 0904-5125-59

SudoGest™
NASAL DECONGESTANT 60 mg
Pseudoephedrine Hydrochloride 60 mg
Relieves Nasal and Sinus Congestion due to Colds or Hay Fever
Without Drowsiness

100 TABLETS

Distributed by MAJOR® PHARMACEUTICALS
31778 Enterprise Drive
Livonia, MI 48150 USA Rev. 01/13 M-17
50844 REV0712N11312

TAMPER EVIDENT: DO NOT USE IF IMPRINTED SAFETY SEAL UNDER CAP IS BROKEN OR MISSING

Major 44-113